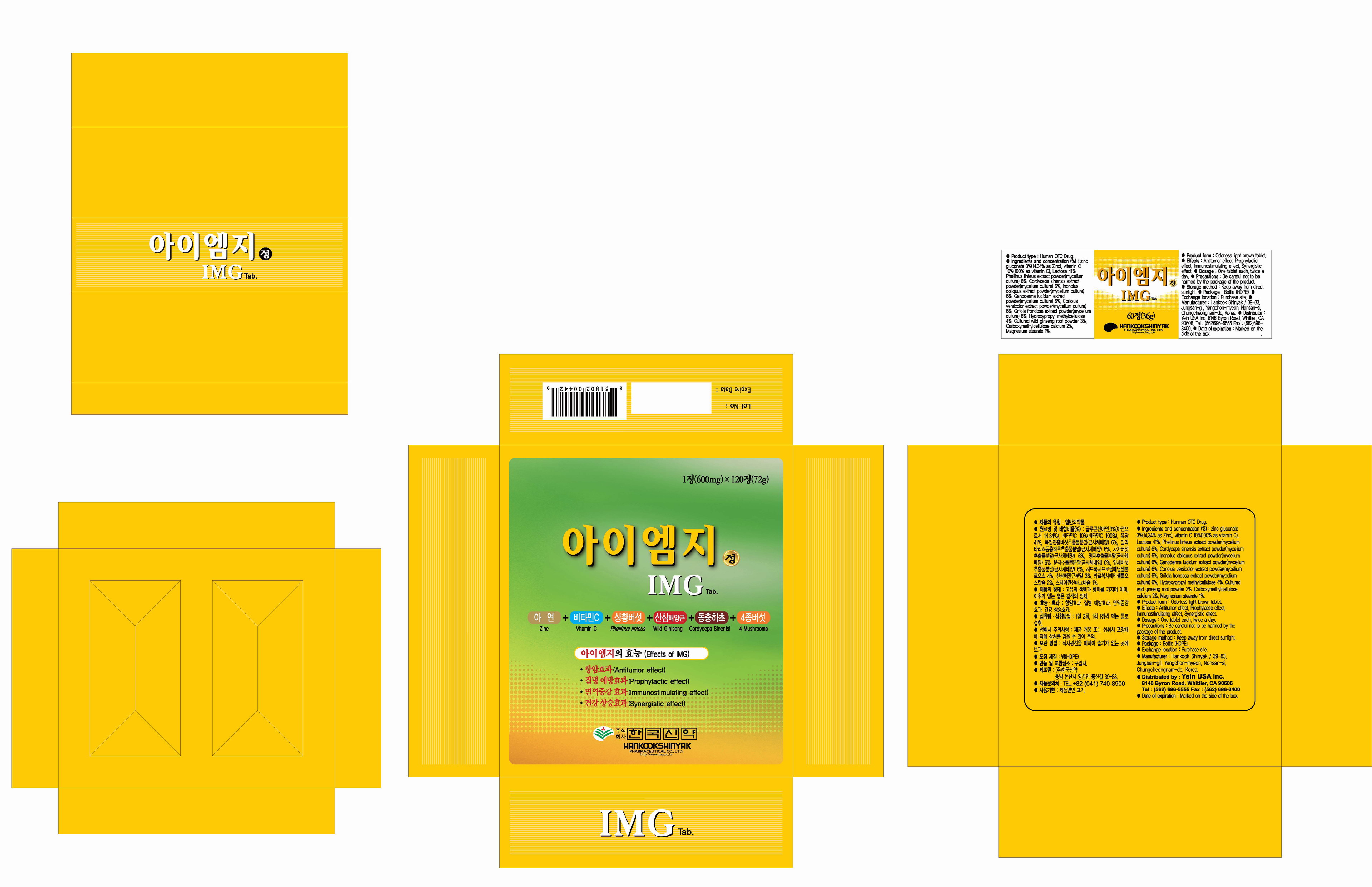 DRUG LABEL: IMG
NDC: 53144-3001 | Form: TABLET
Manufacturer: Yein Trading & Global Co., Ltd
Category: otc | Type: HUMAN OTC DRUG LABEL
Date: 20130226

ACTIVE INGREDIENTS: PHELLINUS LINTEUS MYCELIUM 0.022 1/1 1
INACTIVE INGREDIENTS: ZINC GLUCONATE; ASCORBIC ACID; LACTOSE; REISHI; TRAMETES VERSICOLOR FRUITING BODY; GRIFOLA FRONDOSA WHOLE; HYPROMELLOSES; CARBOXYMETHYLCELLULOSE CALCIUM; MAGNESIUM STEARATE

Drug Facts

ACTIVE INGREDIENT

phellinus linteus mycelium

INACTIVE INGREDIENT

Zinc gluconate 3% (14.34% as Zinc), Vitamin C 10% (100% as vitamin C), Lactose 41%, Cordyceps militaris extract powder (mycelium culture) 6%, Chaga mushroom extract powder (mycelium culture) 6%, Ganoderma lucidum extract powder (mycelium culture) 6%, Trametes versicolor extract powder (mycelium culture) 6%, Grifola frondosa (mycelium culture) 6%, Hydroxypropylmethyl-cellulose 4%, Cultured Wild ginseng root powder 3%, Carboxymethylcellulose calcium 2%, Magnesium stearate 1%

PURPOSE

antitumor effect
prophylactic effect
immunostimulating effect
synergistic effect

keep out of reach of the children

INDICATIONS AND USAGE

1. ulterine hemorrhage and hysterorrhea, dysmenorrhea, intestinal hemorrhage, activation of five organs and stomach function, detoxication
2. reinforcement of immune function by administration in parallel with any chemical therapy after any excising operation form the patient with cancer in digestive system or liver

WARNINGS

- digestive system: occasionally, vomiturition, vomiting, loss of appetite and diarrhea might occur, and infrequently malaise in stomach might take place
- the others: dizziness (1 case), headache (1 case), constipation (3 cases) were reported in clinical test of this medicine

DOSAGE AND ADMINISTRATION

- uterine hemorrhage and hysterorrhea, dysmenorrhea, intestinal hemorrhage, activation of five organs and stomach function, detoxication : as a phellinus linteus mycelia extracts, administer 550~1100mg 2 times per a day before having a meal by mouth
- reinforcement of immune function by administration in parallel with any chemical therapy after any excising operation for the patient with cancer in digestive system or liver : as a phellinus linteus mycelia extracts, administer 1100mg 3 times per a day after having a meal by mouth